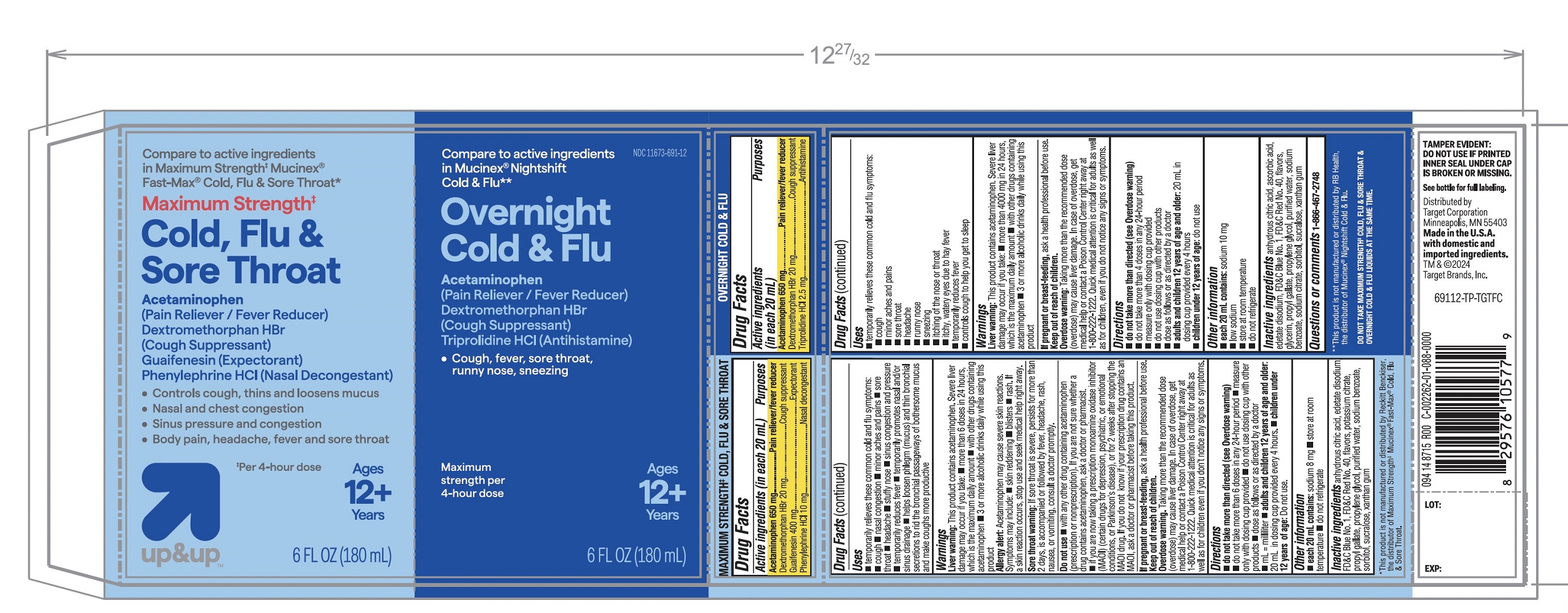 DRUG LABEL: Target Maximum Strength Cold Flu and Sore Throat

NDC: 11673-691 | Form: KIT | Route: ORAL
Manufacturer: TARGET CORPORATION
Category: otc | Type: HUMAN OTC DRUG LABEL
Date: 20251105

ACTIVE INGREDIENTS: ACETAMINOPHEN 650 mg/20 mL; DEXTROMETHORPHAN HYDROBROMIDE 20 mg/20 mL; GUAIFENESIN 400 mg/20 mL; PHENYLEPHRINE HYDROCHLORIDE 10 mg/20 mL; ACETAMINOPHEN 650 mg/20 mL; DEXTROMETHORPHAN HYDROBROMIDE 20 mg/20 mL; TRIPROLIDINE HYDROCHLORIDE 2.5 mg/20 mL
INACTIVE INGREDIENTS: ANHYDROUS CITRIC ACID; EDETATE DISODIUM; FD&C BLUE NO. 1; FD&C RED NO. 40; POTASSIUM CITRATE; PROPYLENE GLYCOL; PROPYL GALLATE; WATER; SODIUM BENZOATE; SORBITOL; SUCRALOSE; XANTHAN GUM; ANHYDROUS CITRIC ACID; ASCORBIC ACID; EDETATE DISODIUM; FD&C BLUE NO. 1; FD&C RED NO. 40; GLYCERIN; PROPYL GALLATE; PROPYLENE GLYCOL; WATER; SODIUM BENZOATE; SODIUM CITRATE, UNSPECIFIED FORM; SORBITOL; SUCRALOSE; XANTHAN GUM

Maximum Strength Cold, Flu & Sore Throat and Overnight Cold & Flu Value Pack

Drug Facts

ACTIVE INGREDIENT

PURPOSE

Active ingredients (in each 20 mL) MAXIMUM STRENGTH‡COLD, FLU & SORE THROAT | Purposes
Acetaminophen 650 mg; Dextromethorphan HBr 20 mg | Pain reliever/fever reducer; Cough suppressant
Guaifenesin 400 mg; Phenylephrine HCl 10 mg | Expectorant; Nasal decongestant

Active ingredients (in each 20 mL) | Purposes
MAXIMUM STRENGTH OVERNIGHT COLD & FLU
Acetaminophen 650 mg | Pain reliever/fever reducer
Dextromethorphan HBr 20 mg; Triprolidine HCl 2.5 mg | Cough suppressant; Antihistamine

Uses

MAXIMUM STRENGTH COLD, FLU & SORE THROAT

- temporarily relieves these common cold and flu symptoms:
- cough
- nasal congestion
- minor aches and pains
- sore throat
- headache
- stuffy nose
- sinus congestion and pressure
- temporarily reduces fever
- temporarily promotes nasal and for sinus drainage
- helps loosen phlegm (mucus) and thin bronchial secretions to rid the bronchial passageways of bothersome mucus and make coughs more productive

Warnings

Liver warnings:This product contains acetaminophen. Severe liver damage may occur if you take:

- more than6 doses in 24 hours which is the maximum daily amount
- with other drugs containing acetaminophen
- 3 or more alcoholic drinks daily while using this product

Allergy alert:Acetaminophen may cause severe skin reactions. Symptoms may include:

- skin reddening
- blisters
- rash. if a skin reaction occurs, stop use and seek medical help right away.

Sore throat warnings:If sore throat is severe, persists for more than 2 days is accompanied or followed by fever, headache, rash, nausea or vomiting consult a doctor promptly.

Do not use

- with any other drug containing acetaminophen (prescription or nonprescription). If you are not sure whether a drug contains acetaminophen, ask a doctor or pharmacist.
- if you are now taking a prescription monoamine oxidase inhibitor (MAOI) (certain drugs for depression, psychiatric, or emotional conditions, or Parkinson's disease), or for 2 weeks after stopping the MAOI drug. If you do not know if your prescription drug contains an MAOI, ask a doctor or pharmacist before taking this product.

Overdose warnings.

Taking more than the recommended dose (overdose) may cause liver damage. In case of overdose, get medical help or contact a Poison Control Center right away at 1-800-222-1222. Quick medical attention is critical for adults as well as for children even if you don’t notice any signs or symptoms.

Directions

- do not take more than directed (see Overdose warning)
- do not take more than 6 doses in any 24- hour period
- measure only with dosing cup provided
- do not use dosing cup with other products
- dose as follows or as directed by a doctor
- mL = milliliter
- adults and children 12 years of age and over:20 mL in dosing cup provided every 4 hours
- children under 12 years of age:Do not use

Other information

- each 20 mL contains:sodium 8 mg
- store at room temperature
- do not refrigerate

Inactive ingredients (Maximum strength Cold, Flu and Sore Throat)

anhydrous citric acid, edetate disodium, FD&C Blue No.1, FD&C Red No. 40, flavors, potassium citrate, propylene glycol, propyl gallate, purified water, sodium benzoate, sorbitol, sucralose, xanthan gum

Uses (OVERNIGHT COLD & FLU

- temporarily relieves these common cold and flu symptoms:
- cough
- minor aches and pains
- sore throat
- headache
- runny nose
- sneezing
- itching of the nose or throat
- itchy, watery eyes due to hay fever
- temporarily reduces fever
- controls cough to help you get to sleep

Warnings

Liver warnings:This product contains acetaminophen. Severe liver damage may occur if you take:

- more than 4000 mg in 24 hours, which is the maximum daily amount
- with other drugs containing acetaminophen
- 3 or more alcoholic drinks daily while using this product

If pregnant or breast feeding

ask a health professional before use

Keep out of reach of children

Overdose warning:Taking more than the recommended dose (overdose) may cause liver damage. In case of overdose, get medical help or contact a Poison Control Centre right away at 1-800-222-1222.

Quick medical attention is critical for adults as well as for children, even if you do not notice any signs

Directions

- do not take more than directed (see overdose warnings
- do not take more than 4 doses in any 24-hour period
- measure only with dosing cup provided
- do not use dosing cup with other products
- dose as follows or as directed by a doctor
- adults and children 12 years of age and over:20 ml in dosing cup provided every 4 hours
- children under 12 years of age:do not use

Other Information

- each 20 mL contains:sodium 10 mg
- low sodium
- store at room temperature
- do not refrigerate

Inactive ingredients (Overnight Cold & Flu)

anhydrous citric acid, ascorbic acid, edetate disodium, FD&C Blue No. 1, FD&C Red No. 40, flavors, glycerin, propyl gallate, propylene glycol, purified water, sodium benzoate, sodium citrate, sorbitol, sucralose and xanthan gum

Questions or comments?

(1-866-467-2748)

PRINCIPAL DISPLAY PANEL - Kit Carton

VALUE PACK

NDC 11673-691-12

Compare to active ingredients Maximum Strength‡Mucinex® Fast Max® Cold, Flu and Sore Throat

Maximum Strength‡

Cold, Flu and Sore Throat

Acetaminophen• Pain Reliever/Fever Reducer

Dextromethorphan HBr • Cough Suppressant
Guaifenesin • Expectorant

Phenylephrine HCl • Nasal Decongestant

- Controls Cough, Thins & Loosens Mucus
- Nasal & Chest Congestion
- Sinus pressure & Congestion
- Body Pain, Headache, Fever & Sore Throat

*Per 4-hour dose

For Ages 12+

6 FL. OZ. (180 mL)

*This product is not manufactured or distributed by Reckitt Benckiser, the distributor of Maximum Strength Mucinex® Fast-Max® Cold, Flu & Sore Throat.

Compare to Mucinex® Nightshift Cold, Flu & Sore Throat Active Ingredients**

Overnight Cold & Flu

Acetaminophen• Pain Reliever/Fever Reducer
Dextromethorphan HBr • Cough Suppressant

Triprolidine HCl • Antihistamine

Night Time Relief for a Better Morning

Maximum Strength per 4-hour dose

- Cough
- Fever
- Sore Throat
- Runny Nose
- Sneezing

For Ages 12+

6 FL OZ (180 mL)

**This product is not manufactured or distributed by RB Health, the distributor of Mucinex® Nightshift Cold & Flu.

TAMPER EVIDENT: DO NOT USE IF PRINTED INNER SEAL UNDER CAP IS BROKEN OR MISSING.

See bottle for full labeling

Distributed by:

094 14 8715 R00

C-001227-01-055

Dist. By Target Corp.

Mpls., MN 55403

TM & © 2020

Target Brands, Inc.

Questions?

Cal 1-866-467-2748

DO NOT TAKE MAXIMUM STRENGTH COLD, FLU & SORE THROAT & OVERNIGHT COLD & FLU LIQUIDS AT THE SAME TIME.